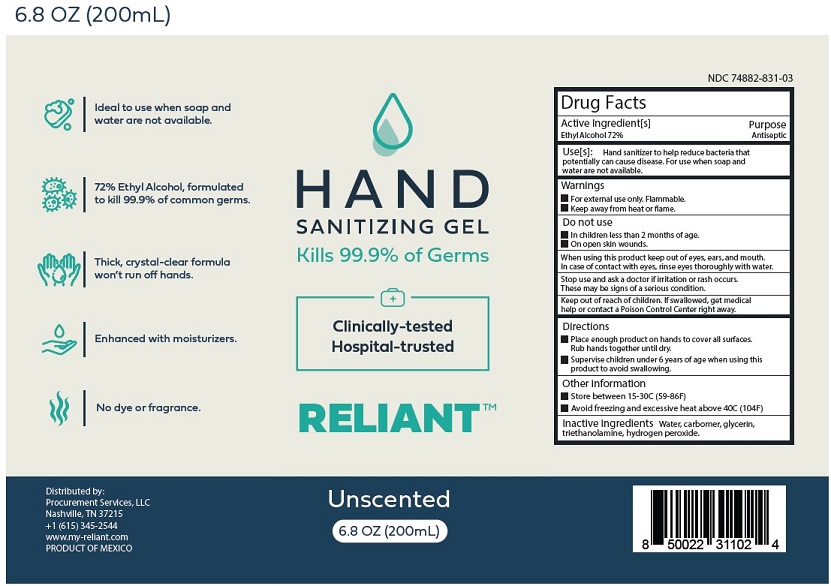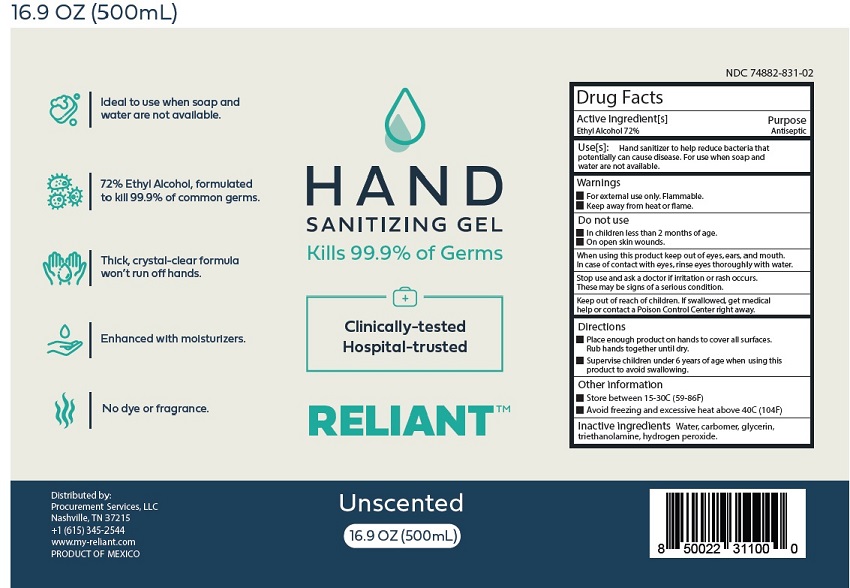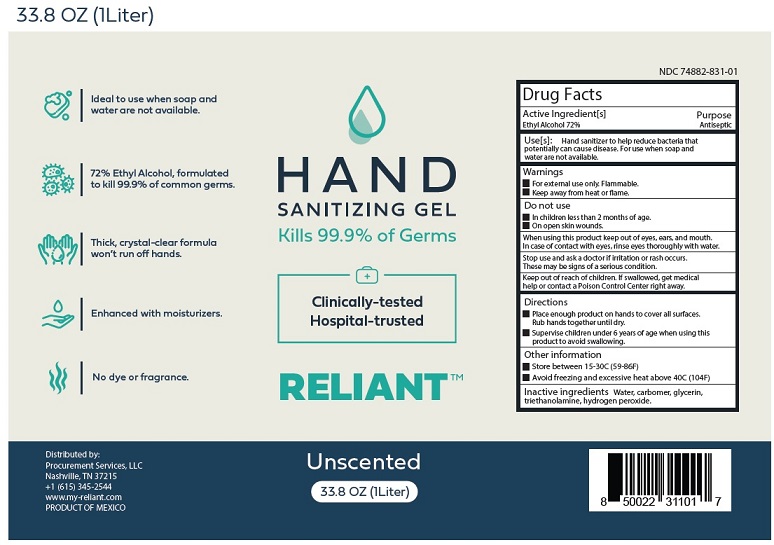 DRUG LABEL: RELIANT Hand Sanitizing Gel
NDC: 74882-831 | Form: GEL
Manufacturer: Procurement Services LLC
Category: otc | Type: HUMAN OTC DRUG LABEL
Date: 20200811

ACTIVE INGREDIENTS: ALCOHOL 72 L/100 L
INACTIVE INGREDIENTS: WATER; CARBOMER HOMOPOLYMER, UNSPECIFIED TYPE; GLYCERIN; TROLAMINE; HYDROGEN PEROXIDE

RELIANT Hand Sanitizing Gel

Drug Facts

Active ingredient[s]

Ethyl Alcohol 72%

Purpose

Antiseptic

INDICATIONS AND USAGE

Use[s]
Hand sanitizer to help reduce bacteria that potentially
can cause disease. For use when soap and water are not available.

Warnings
■ For external use only. Flammable.
■ Keep away from heat or flame.

Do not use
■ In children less than 2 months of age
■ On open skin wounds

When using this product keep out of eyes, ears, and mouth.
In case of contact with eyes, rinse eyes thoroughly with water.

Stop use and ask a doctor if irritation or rash occurs.
These may be signs of a serious condition.

Keep out of reach of children. If swallowed, get medical help
or contact a Poison Control Center right away.

Directions
■ Place enough product on hands to cover all surfaces.
Rub hands together until dry.
■ Supervise children under 6 years of age when using this
product to avoid swallowing.

Other information
■ Store between 15-30C (59-86F)
■ Avoid freezing and excessive heat above 40C (104F)

Inactive ingredients Water, carbomer, glycerin,
triethanolamine, hydrogen peroxide.

Package Labeling - Principal Display Panel

HAND

SANITIZING GEL

Kills 99.9% of Germs

Clinically-tested

Hospital-trusted

RELIANT

Unscented

33.8 OZ (1L)

Distributed by
Procurement Services LLC
Nashville, TN 37215
+1 (615) 345-2544
www.my-reliant.com

PRODUCT OF MEXICO

NDC 74882-831-01

8 60003 64606 9

1 Liter Bottle

500 mL Bottle

200mL Bottle

res